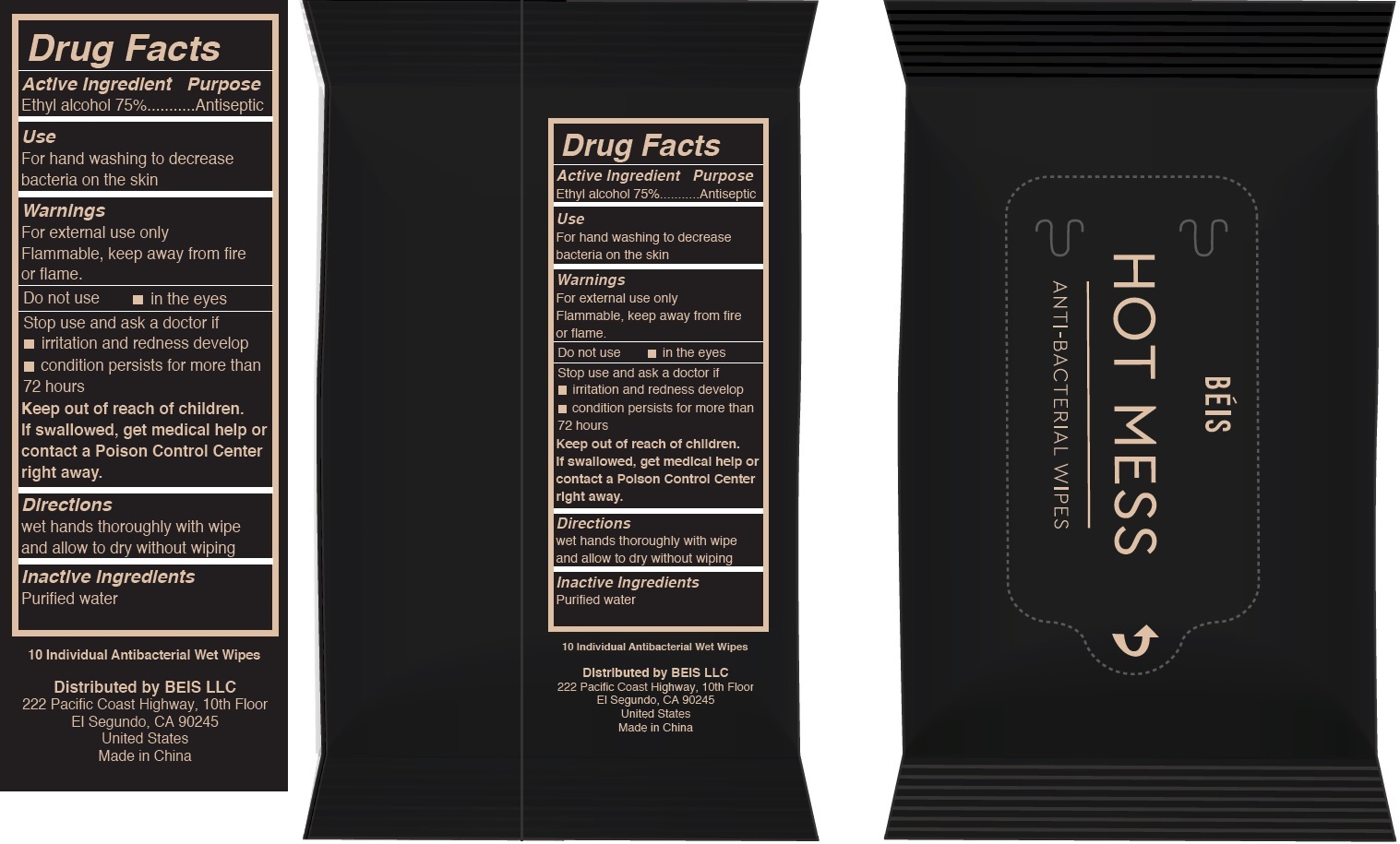 DRUG LABEL: BEIS Hot Mess Antibacterial Wipes
NDC: 81263-002 | Form: CLOTH
Manufacturer: Beis LLC
Category: otc | Type: HUMAN OTC DRUG LABEL
Date: 20211123

ACTIVE INGREDIENTS: ALCOHOL 75 mL/100 mL
INACTIVE INGREDIENTS: WATER

BEIS Hot Mess Antibacterial Wipes

Active Ingredient

Ethyl alcohol 75%

Purpose

Antiseptic

Use

For hand washing to decrease bacteria on the skin

Warnings

For external use only

Flammable, keep away from fire or flame.

Do not use

- in the eyes

Stop use and ask a doctor if

- irritation and redness develop
- condition persists for more than 72 hours

Keep out of reach of children.

If swallowed, get medical help or contact a Poison Control Center right away.

Directions

wet hands thoroughly with wipe and allow to dry without wiping

Inactive Ingredients

Purified water